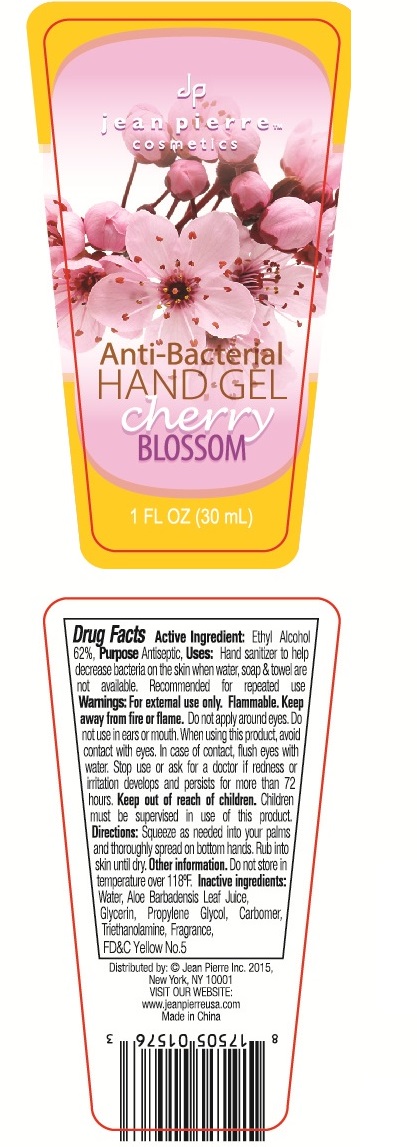 DRUG LABEL: Anti-Bacterial Hand Gel
NDC: 70483-001 | Form: GEL
Manufacturer: Jean Pierre Inc.
Category: otc | Type: HUMAN OTC DRUG LABEL
Date: 20160527

ACTIVE INGREDIENTS: ALCOHOL 62 mL/100 mL
INACTIVE INGREDIENTS: WATER; ALOE VERA LEAF; GLYCERIN; PROPYLENE GLYCOL; CARBOMER INTERPOLYMER TYPE A (55000 CPS); TROLAMINE; FD&C YELLOW NO. 5

Active Ingredient: Ethyl Alcohol 62%

Purpose Antiseptic

WARNINGS

Warnings: For external use only. Flammable. Keep away from fire or flame. Do not apply around eyes. Do not use in ears or mouth. When using this product, avoid contact with eyes. In case of contact, flush eyes with water.

Stop use or ask for a doctor if redness or irritation develops and persists for more than 72 hours.

Keep out of reach of children. Children must be supervised in use of this product.

DOSAGE AND ADMINISTRATION

Directions: Squeeze as needed into your palms and thoroughly spread on bottom hands. Rub into skin until dry.

INACTIVE INGREDIENT

Inactive ingredients: Water, Aloe Barbadenis Leaf, Glycerin, Propylene Glycol, Carbomer, Triethanolamine, Fragrance, FD&C Yellow No.5

INDICATIONS AND USAGE

Uses: Hand sanitizer to help decrease bacteria on the skin when water, soap & towel are not available. Recommended for repeated use

Other information

Do not store in temperature over 118 F.